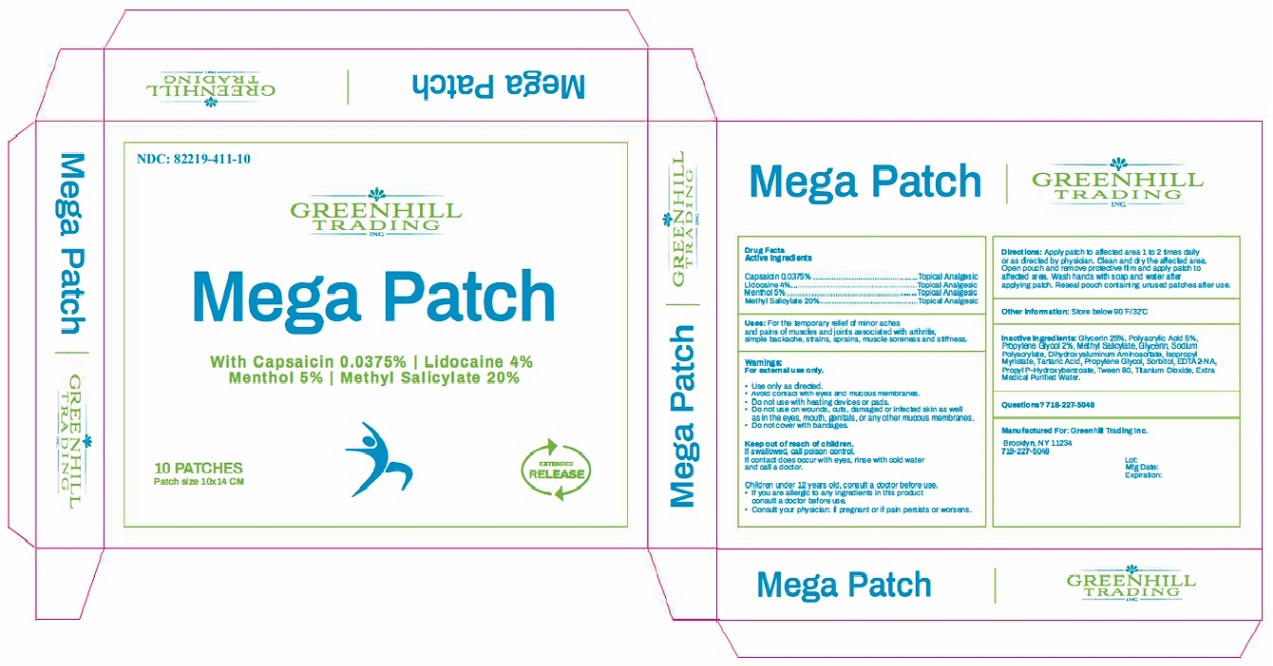 DRUG LABEL: Mega Patch
NDC: 82219-411 | Form: PATCH
Manufacturer: GREENHILL TRADING, INC.
Category: otc | Type: HUMAN OTC DRUG LABEL
Date: 20230821

ACTIVE INGREDIENTS: CAPSAICIN 0.0375 g/1 1; LIDOCAINE 4 g/1 1; MENTHOL 5 g/1 1; METHYL SALICYLATE 20 g/1 1
INACTIVE INGREDIENTS: GLYCERIN; POLYACRYLIC ACID (450000 MW); PROPYLENE GLYCOL; SODIUM POLYACRYLATE (2500000 MW); DIHYDROXYALUMINUM AMINOACETATE; ISOPROPYL MYRISTATE; TARTARIC ACID; SORBITOL; EDETATE DISODIUM; PROPYLPARABEN; POLYSORBATE 80; TITANIUM DIOXIDE; WATER

Mega Patch With Capsaicin 0.0375%, Lidocaine 4%, Menthol 5%, Methyl Salicylate 20%

Drug Facts Active Ingredients

Capsaicin 0.0375%

Lidocaine 4%

Menthol 5%

Methyl Salicylate 20%

PURPOSE

Topical Analgesic

INDICATIONS AND USAGE

Uses: For the temporary relief of minor aches and pains of muscles and joints associated with arthritis, simple backache, strains, sprains, muscle soreness and stiffness.

Warnings:

For external use only.

- Use only as directed.
- Avoid contact with eyes and mucous membranes.
- Do not use with heating devices or pads.
- Do not use on wounds, cuts, damaged or infected skin as well as in the eyes, mouth, genitals, or any other mucous membranes.
- Do not cover with bandages.

Keep out of reach of chlidren.

If swallowed, call poison control.

If contact does occur with eyes, rinse with cold water and call a doctor.

WARNINGS AND PRECAUTIONS

Children under 12 years old, consult a doctor before use.

- If you are allergic to any ingredients in this product consult a doctor before use.
- Consult your physician: If pregnant or if pain persists or worsens.

DOSAGE AND ADMINISTRATION

Directions: Apply patch to affected area 1 to 2 times daily or as directed by physician. Clean and dry the affected area. Open pouch and remove protective film and apply patch to affected area. Wash hands with soap and water after applying patch. Reseal pouch containing unused patches after use.

Other information: Store below 90°F/32°C

INACTIVE INGREDIENT

Inactive Ingredients: Glycerin 25%, Polyacrylic Acid 5%, Propylene Glycol 2%, Methyl salicylate, Glycerin, Sodium Polyacrylate, Dihydroxyaluminum Aminoacetate, Isopropyl Myristate, Tartaric Acid, Propylene Glycol, Sorbitol, EDTA2-NA, Propyl P-Hydroxybenzoate, Tween 80, Titanium Dioxide, Extra Medical Purified Water.

Questions? 718-227-5048

Manufactured For: Greenhill Trading Inc.

Brooklyn, NY 11234
718-227-5048

PRINCIPAL DISPLAY PANEL

NDC: 82219-411-10

GREENHILL
TRADING
INC

Mega Patch

With Capsaicin 0.0375%, Lidocaine 4%,
Menthol 5%, Methyl Salicylate 20%

10 PATCHES
Patch size 10x14 CM

EXTENDED
RELEASE